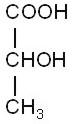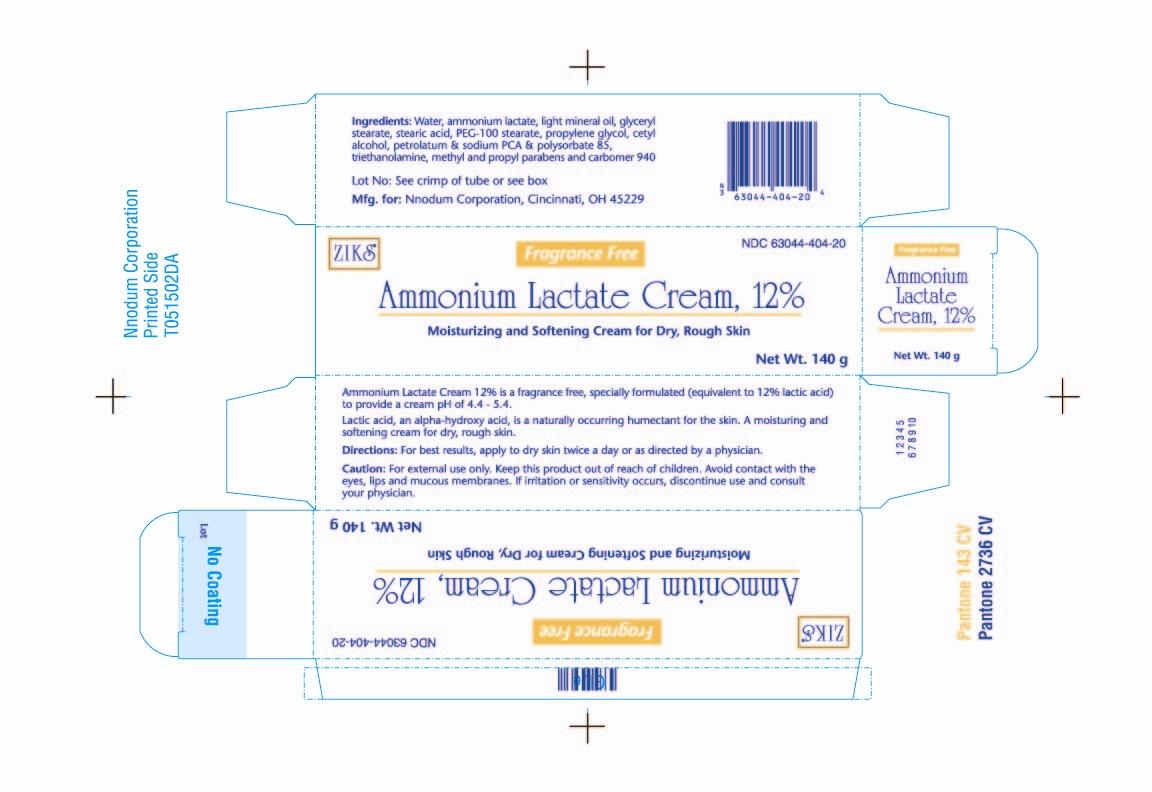 DRUG LABEL: Ammonium Lactate
NDC: 63044-404 | Form: CREAM
Manufacturer: Nnodum Pharmaceuticals
Category: otc | Type: HUMAN OTC DRUG LABEL
Date: 20091230

ACTIVE INGREDIENTS: AMMONIUM LACTATE 17 g/1 g
INACTIVE INGREDIENTS: CETYL ALCOHOL; GLYCERIN; GLYCERYL MONOSTEARATE; LIGHT MINERAL OIL; MAGNESIUM ALUMINUM SILICATE; PROPYLENE OXIDE; CARBOMER HOMOPOLYMER TYPE C; POLYSORBATE 80; TROLAMINE; PROPYLENE GLYCOL; PETROLATUM; SODIUM PYRROLIDONE CARBOXYLATE; STEARIC ACID; WATER

Ammonium Lactate Cream

63044-404-20

For Dermatologic use only.

Not for Ophthalmic, Oral or Intravaginal use.

DESCRIPTION

Ammonium Lactate Cream, 12% is a formulation of 12% lactic acid neutralized with ammonium hydroxide, as ammonium lactate with a pH of 4.4-5.4.

Ingredients: Ammonium Lactate Cream, 12% also contains cetyl alcohol, glycerin, glyceryl stearate, light mineral oil, magnesium aluminum silicate, methyl and propyl parabens, Carbomer 940, PEG-100 stearate, polysorbate 85, triethanolamine, propylene glycol, Petrolatum and Sodium PCA, stearic acid and water.

Lactic acid is a racemic mixture of 2-hydroxypropanoic acid and has the following structural formula:

CLINICAL PHARMACOLOGY

Lactic acid is an alpha-hydroxy acid. It is a normal constituent of tissues and blood. The alpha-hydroxy acids (and their salts) may act as humectants when applied to the skin. This property may influence hydration of the stratum corneum. In addition, lactic acid, when applied to the skin, may act to decrease corneocyte cohesion. The mechanism(s) by which this is accomplished is not yet known.

An in vitro study of percutaneous absorption of Ammonium Lactate Cream using human cadaver skin indicates that approximately 5.8% of the material was absorbed after 68 hours.

INDICATIONS AND USAGE

Ammonium Lactate Cream is indicated for the treatment of dry, scaly skin (xerosis) and ichthyosis vulgaris and for temporary relief of itching associated with these conditions.

CONTRAINDICATIONS

Ammonium Lactate Cream is contraindicated in those patients with a history of hypersensitivity to any of the label ingredients.

WARNING

Sun exposure to areas of the skin treated with Ammonium lactate Cream, 12% should be minimized or avoided (see PRECAUTIONS). The use of Ammonium Lactate Cream should be discontinued if any hypersensitivity is observed.

PRECAUTIONS

General

For external use only. Stinging or burning may occur when applied to skin with fissures, erosions, or that is otherwise abraded (for example, after shaving the legs). Caution is advised when used on the face because of the potential for irritation. The potential for post-inflammatory hypo- or hyperpigmentation has not been studied.

Information For Patients

Patients using Ammonium lactate Cream, 12% should receive the following information and instructions:

1).This medication is to be used as directed by the physician, and should not be used for any disorder other than for which it was prescribed. It is for external use only. Avoid contact with eyes, lips, or mucous membranes.

2).Patients should minimize or avoid use of this product on areas of the skin that may be exposed to natural or artificial sunlight, including the face. If sun exposure is unavoidable, clothing should be worn to protect the skin.

3).This medication may cause transient stinging or burning when applied to skin with fissures, erosions, or abrasions (for example, after shaving the legs).

4).If the skin condition worsens with treatment, the medication should be promptly discontinued

Carcinogenesis, Mutagenesis, Impairment of Fertility

The topical treatment of CD-1 mice with 12%, 21% or 30% ammonium lactate formulations for two years did not produce a significant increase in dermal or systemic tumors in the absence of increased exposure to ultraviolet radiation. The maximum systemic exposure of the mice in this study was 0.7 times the maximum possible systemic exposure in humans. However, a long-term photocarcinogenicity study in hairless albino mice suggested that topically applied 12% ammonium lactate formulations enhanced the rate of ultraviolet light-induced skin tumor formation.

The mutagenic potential of ammonium lactate formulations was evaluated in the Ames assay and in the mouse in vivo micronucleus assay, both of which were negative.

In dermal Segment I and III studies with ammonium lactate formulations there were no effects observed in fertility or pre- or post-natal development parameters in rats at dose levels of 300 mg/kg/day (1800 mg/m2/day), approximately 0.4 times the human topical dose.

Pregnancy

Teratogenic Effects :Pregnancy Category B.

Animal reproduction studies have been performed in rats and rabbits at doses up to 0.7 and 1.5 times the human dose, respectively (600 mg/kg/day, corresponding to 3600 mg/m2/day in the rat and 7200 mg/m2/day in the rabbit) and have revealed no evidence of impaired fertility or harm to the fetus due to ammonium lactate formulations. There are, however, no adequate and well-controlled studies in pregnant women. Because animal reproduction studies are not always predictive of human response, Ammonium Lactate Cream should be used during pregnancy only if clearly needed.

Nursing Mothers

Although lactic acid is a normal constituent of blood and tissues, it is not known to what extent this drug affects normal lactic acid levels in human milk. Because many drugs are excreted in human milk, caution should be exercised when Ammonium Lactate Cream is administered to a nursing woman.

Pediatric Use

Safety and effectiveness of Ammonium Lactate Cream have been demonstrated in infants and children. No unusual toxic effects were reported.

Geriatric Use

Clinical studies of Ammonium lactate Cream, 12% did not include sufficient numbers of subjects aged 65 and over to determine whether they respond differently from younger subjects. Other reported clinical experience has not identified differences in responses between elderly and younger patients. In general, dose selection for an elderly patient should be cautious.

ADVERSE REACTIONS

The most frequent adverse experiences in patients with xeroxis are transient stinging (1 in 30 patients), burning (1 in 30 patients), erythema (1 in 50 patients) and peeling (1 in 60 patients). Other adverse reactions which occur less frequently are irritation, eczema, petechiae, dryness and hyperpigmentation.

Due to more severe initial skin conditions associated with ichthyosis, there was a higher incidence of transient stinging, burning and erythema (each occurring in 1 in 10 patients).

OVERDOSAGE

The oral administration of Ammonium Lactate Cream to rats and mice showed this drug to be practically non-toxic (LD50 > 15 mL/kg).

DOSAGE AND ADMINISTRATION

Shake well. Apply to the affected areas and rub in thoroughly. Use twice daily or as directed by a physician.

HOW SUPPLIED

Ammonium lactate Cream, 12% is available in a 140g (NDC # 63044-404-20) plastic tube.

Store at controlled room temperature 15° C - 30° C (59° F - 86° F).

Manufactured for:
Nnodum Pharmaceuticals
Cincinnati, Ohio 45229
By: EMS Contract Manufacturing

Revised January 2008
Ammonium lactate Lotion